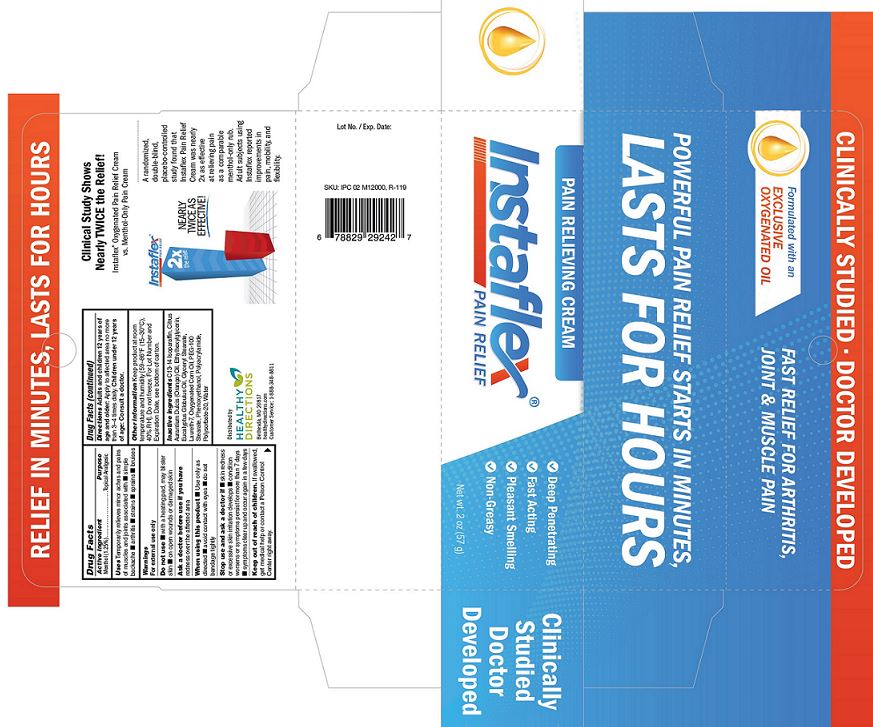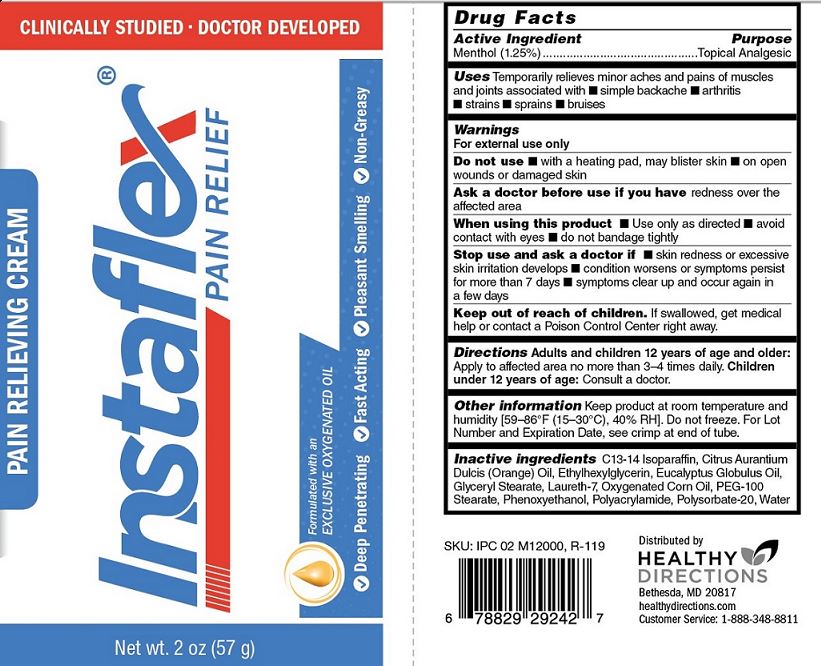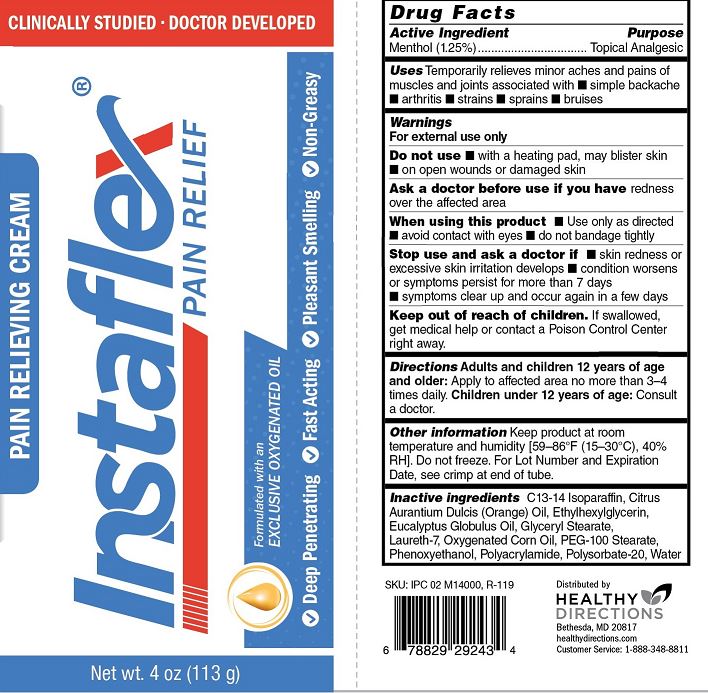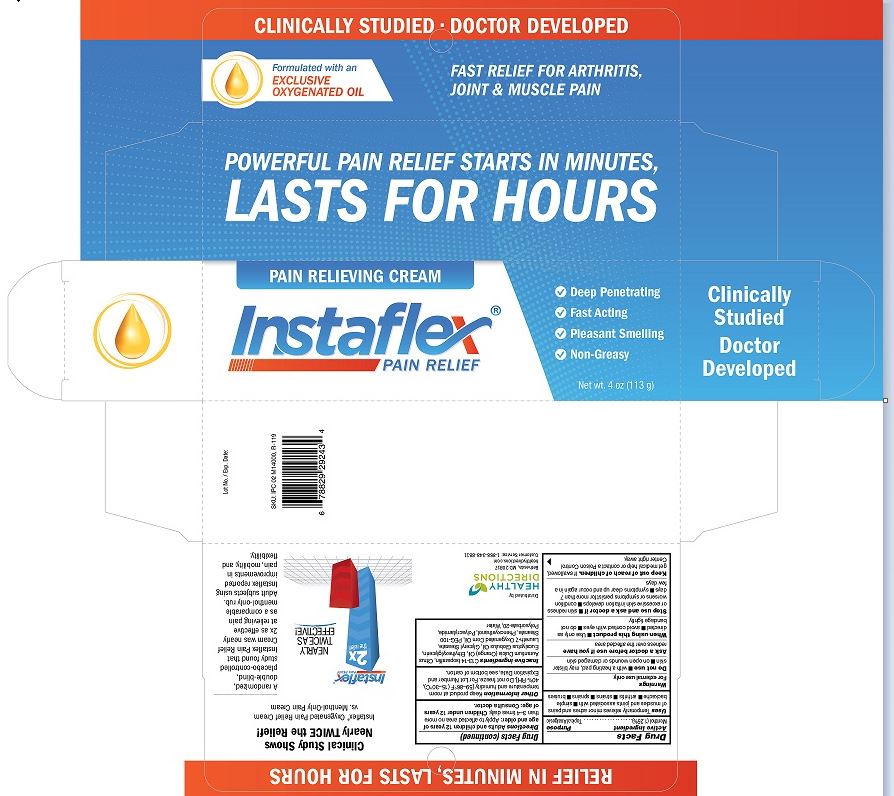 DRUG LABEL: Instaflex Pain Relief Cream
NDC: 70015-665 | Form: CREAM
Manufacturer: Healthy Directions, LLC
Category: otc | Type: HUMAN OTC DRUG LABEL
Date: 20200610

ACTIVE INGREDIENTS: MENTHOL 12.5 mg/1 g
INACTIVE INGREDIENTS: C13-14 ISOPARAFFIN; ORANGE OIL; ETHYLHEXYLGLYCERIN; EUCALYPTUS OIL; GLYCERYL MONOSTEARATE; LAURETH-7; CORN OIL; PEG-100 STEARATE; PHENOXYETHANOL; POLYACRYLAMIDE (CROSSLINKED; 0.01-0.2 MOLE PERCENT BISACRYLAMIDE); POLYSORBATE 20; WATER

Instaflex Pain Relief Cream

Drug Facts

Active Ingredient

Menthol (1.25%)

Purpose

Topical Analgesic

INDICATIONS AND USAGE

Uses Temporarily relieves minor aches and pains

of muscles and joints associated with

- simple backache
- arthritis
- strains
- sprains
- bruises

Warnings

For external use only

Do not use

- with a heating pad, may blister skin
- on open wounds or damaged skin

Ask a doctor before use if you have

redness over the affected area

When using this product

- Use only as directed
- avoid contact with eyes
- do not bandage tightly

Stop use and ask a doctor if

- skin redness or excessive skin irritation develops
- condition worsens or symptoms persist for more than 7 days
- symptoms clear up and occur again in a few days

Keep out of reach of children.

If swallowed, get medical help or contact a Poison Control Center right away.

DOSAGE AND ADMINISTRATION

Directions Adult and children 12 years of

age and older: Apply to affected area no more

than 3-4 times daily. Children under 12 years

of age: Consult a doctor.

Other information

Keep product at room termperature and

humidity [59-86°F (15-30°C), 40% RH]. Do not freeze. For Lot

Number and Expiration Date, see crimp at end of tube.

Inactive ingredients C13-14 Isoparaffin, Citrus Aurantium

Dulcis (Orange) Oil, Ethylhexlglycerin, Eucalyptus Globulus Oil,

Glyceryl Stearate, Laureth-7, Oxygenated Corn Oil, PEG-100

Stearate, Phenoxyethanol, Polyacrylamide, Polysorbate-20, Water

PACKAGE LABEL

PAIN RELIEVING CREAM

Instaflex

PAIN RELIEF

Formulated with an

EXCLUSIVE OXYGENATED OIL

FAST RELIEF FOR ARTHRITIS,

JOINT & MUSCLE PAIN

POWERFUL PAIN RELIEF STARTS IN MINUTES,

LASTS FOR HOURS

Deep Penetrating | Fast Acting | Pleasant Smelling | Non-Greasy

CLINICALLY STUDIED | DOCTOR DEVELOPED

Net wt. [2/4] oz ([57/113] g)